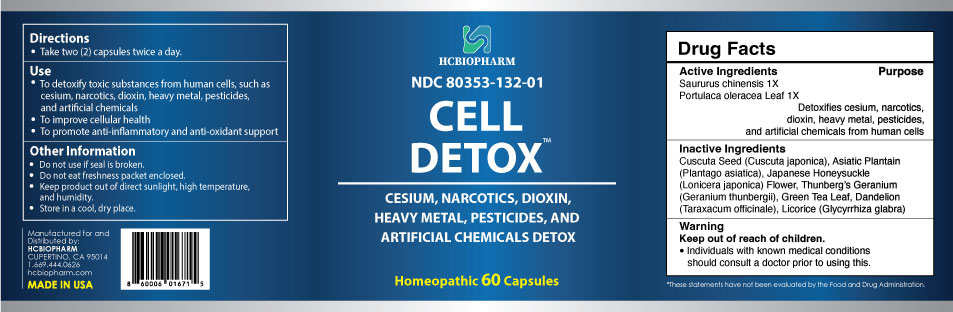 DRUG LABEL: Cell Detox
NDC: 80353-132 | Form: CAPSULE
Manufacturer: HCBIOPHARM LLC
Category: homeopathic | Type: HUMAN OTC DRUG LABEL
Date: 20250103

ACTIVE INGREDIENTS: SAURURUS CHINENSIS WHOLE 1 [hp_X]/1 1; PORTULACA OLERACEA LEAF 1 [hp_X]/1 1
INACTIVE INGREDIENTS: TARAXACUM OFFICINALE; CUSCUTA JAPONICA SEED; GERANIUM THUNBERGII WHOLE; GREEN TEA LEAF; GLYCYRRHIZA GLABRA; PLANTAGO ASIATICA; LONICERA JAPONICA FLOWER

Active Ingredients

Saururus chinensis 1X

Portulaca oleracea Leaf 1X

Purpose

Detoxifies cesium, narcotics, dioxin, heavy metal, pesticides, and artificial chemicals from human cells*

Keep Out of Reach of Children

Directions

Take two (2) capsules twice a day.

Use

- To detoxify toxic substances from human cells, such as cesium, narcotics, dioxin, heavy metal, pesticides, and artificial chemicals
- To improve cellular health
- To promote anti-inflammatory and anti-oxidant support

Inactive Ingredients

Cuscuta (Cuscuta japonica) Seed, Asiatin Plantain (Plantago asiatica), Japanese Honeysuckle (Lonicera japonica) Flower, Thunberg’s Geranium (Geranium thunbergii), Green Tea Leaf, Dandelion (Taraxacum officinale), Licorice (Glycyrrhiza glabra)

Warning

Individuals with known medical conditions should consult a doctor prior to using this.

Other Information

Do not use if seal is broken.
Do not eat freshness packet enclosed.
Keep product out of direct sunlight, high temperature, and humidity.
Store in a cool, dry place.

Package Label Display

Cell Detox

CESIUM, NARCOTICS, DIOXIN, HEAVY METAL, PESTIFICIDES, AND ARTIFICIAL CHEMICALS DETOX

Homeopathic 60 Capsules